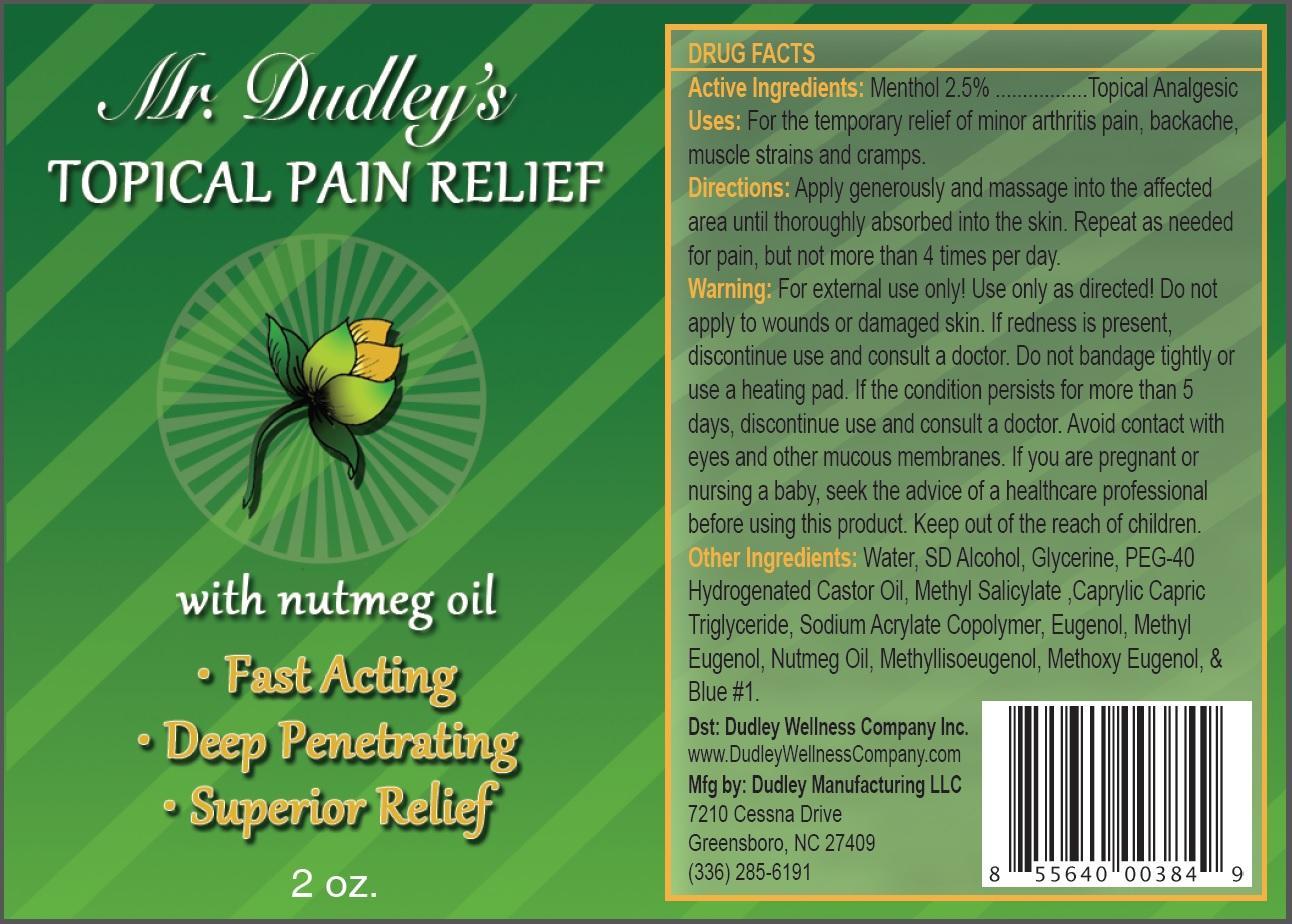 DRUG LABEL: Mr Dudleys Topical Pain Relief
NDC: 58484-100 | Form: CREAM
Manufacturer: DUDLEY WELLNESS COMPANY INC
Category: otc | Type: HUMAN OTC DRUG LABEL
Date: 20130510

ACTIVE INGREDIENTS: MENTHOL 2.5 g/100 g
INACTIVE INGREDIENTS: WATER; ALCOHOL; GLYCERIN; POLYOXYL 40 HYDROGENATED CASTOR OIL; METHYL SALICYLATE; MEDIUM-CHAIN TRIGLYCERIDES; ACRYLAMIDE; EUGENOL; METHYL EUGENOL; NUTMEG OIL; METHYL ISOEUGENOL; 4-ALLYL-2,6-DIMETHOXYPHENOL; FD&C BLUE NO. 1

Drug Facts

Active Ingredient:

Menthol 2.5%

Purpose:

Topical Analgesic

Uses:

For the temporary relief of minor arthritis pain, backache, muscle strains and cramps.

Keep out of the reach of children

Warnings:

- For external use only.
- Use only as directed.
- Do not apply to wounds or damaged skin.
- If redness is present, discontinue use and consult a doctor.
- Do not bandage tightly or use a heating pad.
- If the condition persists for more than 5 days, discontinue use and consult a doctor.
- Avoid contact with eyes and other mucous membranes.
- If you are pregnant or nursing a baby, seek the advice of a healthcare professional before using this product.

Directions:

Apply generously and massage into the affected area until thoroughly absorbed into the skin. Repeat as needed for pain, but not more than 4 times per day.

Inactive Ingredients:

Water, SD Alcohol, Glycerine, PEG-40 Hydrogenated Castor Oil, Methyl Salicylate, Caprylic Capric Triglyceride, Sodium Acrylate Copolymer, Eugenol, Methyl Eugenol, Nutmeg Oil, Methyllisoeugenol, Methoxy Eugenol, Blue #1